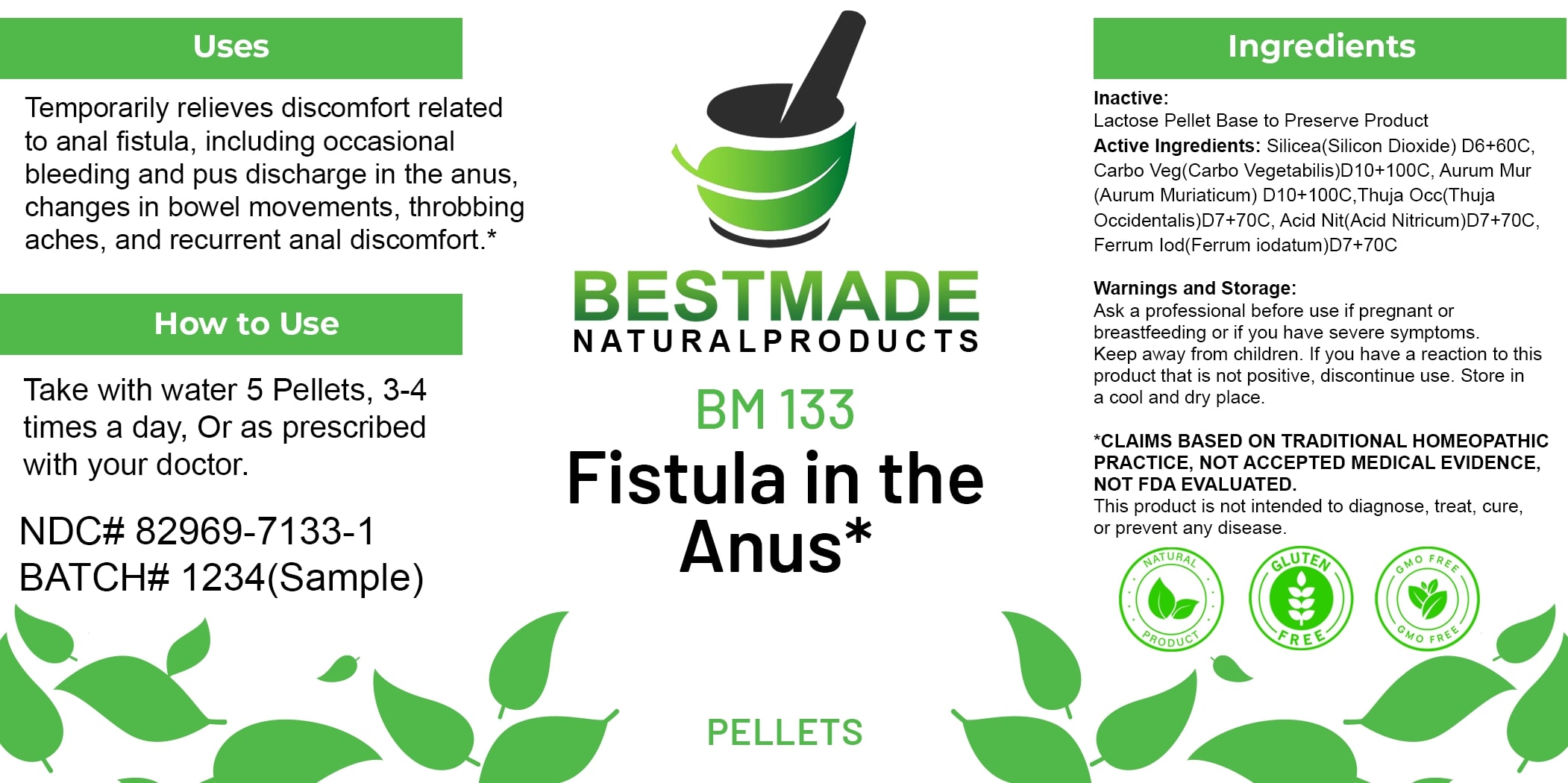 DRUG LABEL: Bestmade Natural Products BM133 Pellets
NDC: 82969-7133 | Form: TABLET, SOLUBLE
Manufacturer: Bestmade Natural Products
Category: homeopathic | Type: HUMAN OTC DRUG LABEL
Date: 20250408

ACTIVE INGREDIENTS: SILICA 30 [hp_C]/30 [hp_C]; THUJA OCCIDENTALIS LEAFY TWIG 30 [hp_C]/30 [hp_C]; FERROUS IODIDE 30 [hp_C]/30 [hp_C]; ACTIVATED CHARCOAL 30 [hp_C]/30 [hp_C]; GOLD TRICHLORIDE 30 [hp_C]/30 [hp_C]; NITRIC ACID 30 [hp_C]/30 [hp_C]
INACTIVE INGREDIENTS: LACTOSE 30 [hp_C]/30 [hp_C]

BM133 Pellets

DOSAGE AND ADMINISTRATION

How to Use

Take with water 5 Pellets, 3-4 times a day, Or as prescribed with your doctor.

INACTIVE INGREDIENT

Ingredients

Inactive: Lactose Pellet Base to Preserve Product

ACTIVE INGREDIENT

Active Ingredients: Silicea(Silicon Dioxide) D6+60C, Carbo Veg(Carbo Vegetabilis)D10+100C, Aurum Mur (Aurum Muriaticum) D10+100C, Thuja Occ(Thuja Occidentalis)D7+70C, Acid Nit(Acid Nitricum)D7+70C, Ferrum Iod(Ferrum Iodatum)D7+70C

Uses

Temporarily relieves discomfort related to anal fistula, including occasional bleeding and pus discharge in the anus, changes in bowel movements, throbbing aches, and recurrent anal discomfort.*

*CLAIMS BASED ON TRADITIONAL HOMEOPATHIC PRACTICE. NOT ACCEPTED MEDICAL EVIDENCE. NOT FDA EVALUATED.

This product is not intended to diagnose, treat, cure, or prevent any disease.

Uses

Temporarily relieves discomfort related to anal fistula, including occasional bleeding and pus discharge in the anus, changes in bowel movements, throbbing aches, and recurrent anal discomfort.*

*CLAIMS BASED ON TRADITIONAL HOMEOPATHIC PRACTICE. NOT ACCEPTED MEDICAL EVIDENCE. NOT FDA EVALUATED.

This product is not intended to diagnose, treat, cure, or prevent any disease.

KEEP OUT OF REACH OF CHILDREN

Warnings and Storage:

Ask a professional before use if pregnant or breastfeeding or if you have severe symptoms. Keep away from children. If you have a reaction to this product that is not positive, discontinue use. Store in a cool and dry place.

Warnings and Storage:

Ask a professional before use if pregnant or breastfeeding or if you have severe symptoms. Keep away from children. If you have a reaction to this product that is not positive, discontinue use. Store in a cool and dry place.

*CLAIMS BASED ON TRADITIONAL HOMEOPATHIC PRACTICE. NOT ACCEPTED MEDICAL EVIDENCE. NOT FDA EVALUATED.

This product is not intended to diagnose, treat, cure, or prevent any disease.

Entire package label